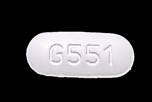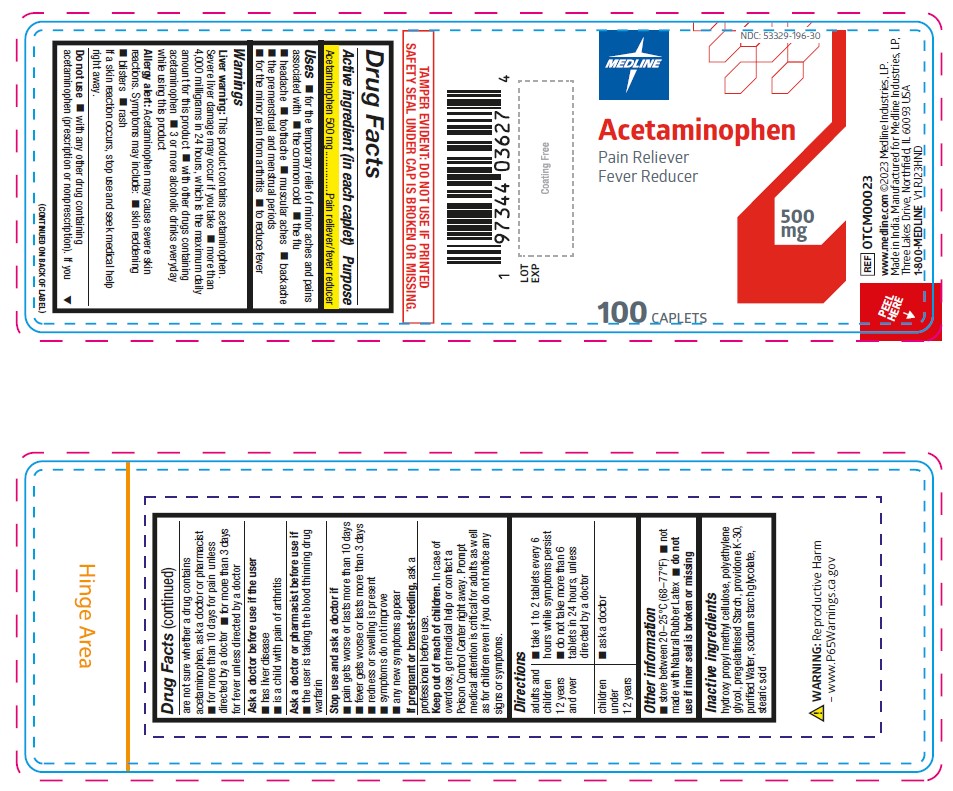 DRUG LABEL: Medline
NDC: 53329-196 | Form: TABLET
Manufacturer: Medline Industries, LP
Category: otc | Type: HUMAN OTC DRUG LABEL
Date: 20250701

ACTIVE INGREDIENTS: ACETAMINOPHEN 500 mg/1 1
INACTIVE INGREDIENTS: STEARIC ACID; WATER; HYDROXYPROPYL METHYLCELLULOSE; POVIDONE K30; POLYETHYLENE GLYCOL, UNSPECIFIED; SODIUM STARCH GLYCOLATE TYPE A; STARCH, CORN

196 OTCM00023 500mg Acetaminophen Cap

Active ingredient (in each caplet)

Acetaminophen 500 mg

Purpose

Pain reliever/fever reducer

Uses

for the temporary relief of minor aches and pains associated with

- the common cold
- the flu
- headache
- toothache
- muscular aches
- backache
- the premenstrual and menstrual periods
- for the minor pain from arthritis
- to reduce fever

Warnings

Liver warning: This product contains acetaminophen.

Severe liver damage may occur if you take

- more than 4,000 milligrams in 24 hours, which is the maximum daily amount for this product
- with other drugs containing acetaminophen
- 3 or more alcoholic drinks everyday while using this product

Allergy alert: Acetaminophen may cause severe skin
reactions. Symptoms may include:

- skin reddening
- blisters
- rash

If a skin reaction occurs, stop use and seek medical help
right away.

Ask a doctor before use if the user

- has liver disease
- is a child with pain of arthritis

Do not use

- with any other drug containing acetaminophen (prescription or nonprescription). If you are not sure whether a drug contains acetaminophen, ask a doctor or pharmacist
- for more than 10 days for pain unless directed by a doctor
- for more than 3 days for fever unless directed by a doctor

Ask a doctor or pharmacist before use if

- the user is taking the blood thinning drug warfarin

Stop use and ask a doctor if

- pain gets worse or lasts more than 10 days
- fever gets worse or lasts more than 3 days
- redness or swelling is present
- symptoms do not improve
- any new symptoms appear

If pregnant or breast-feeding,

ask a professional before use

Keep out of reach of children.

In case of overdose, get medical help or contact a Poison Control Center right away. Prompt medical attention is critical for adults as well as for children even if you do not notice any signs or symptoms.

Directions

adults and children 12 years and over | - take 1 to 2 tablets every 6 hours while symptoms persist - do not take more than 6 tablets in 24 hours, unless directed by a doctor
children under 12 years | - ask a doctor

Other information

- store between 20–25°C (68–77°F)
- not made with Natural Rubber Latex
- do not use if inner seal is broken or missing

Inactive Ingredients

hydroxy propyl methyl cellulose, polyethylene glycol, pregelatinised Starch, providone K-30, purified Water, sodium starch glycolate,
stearic acid